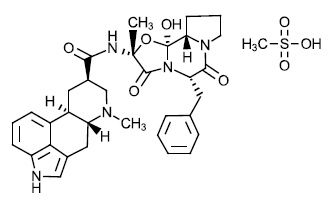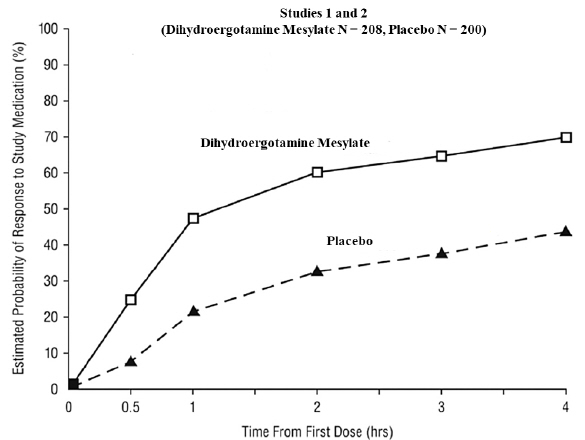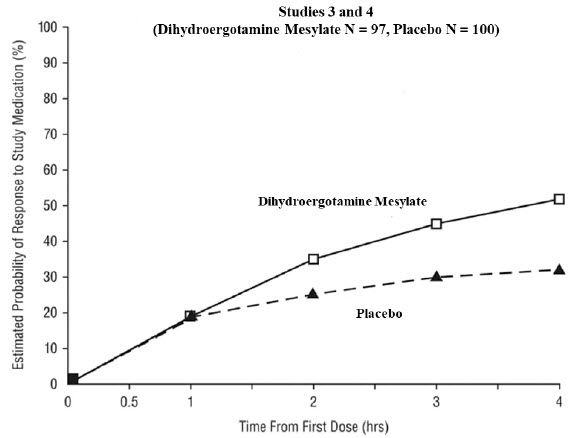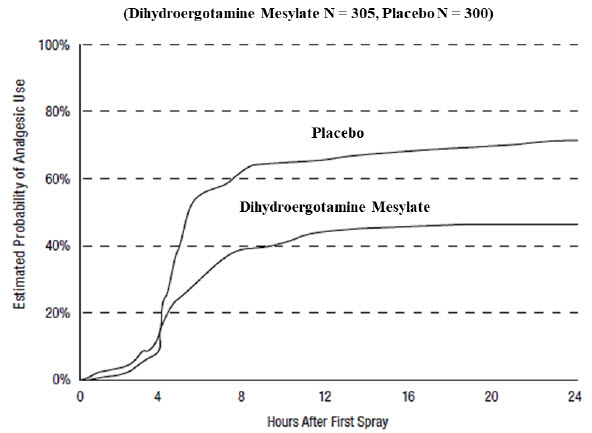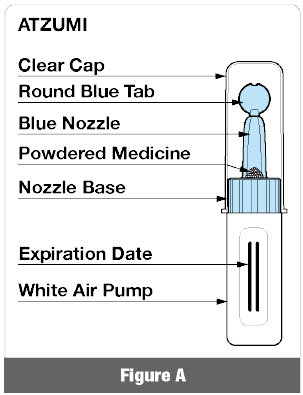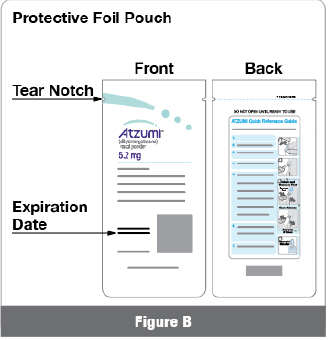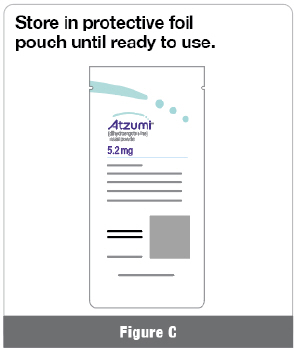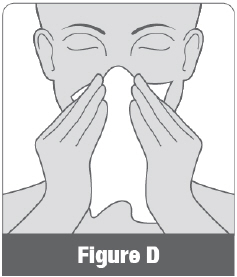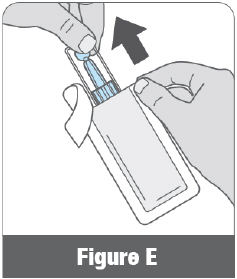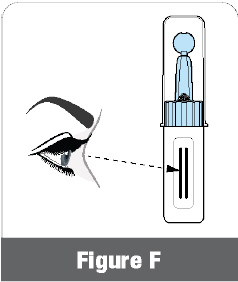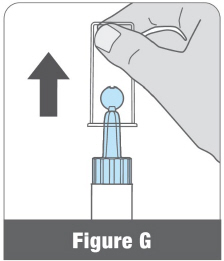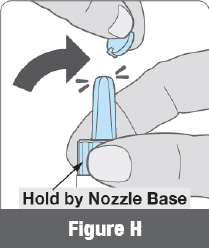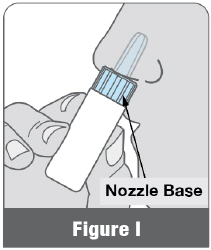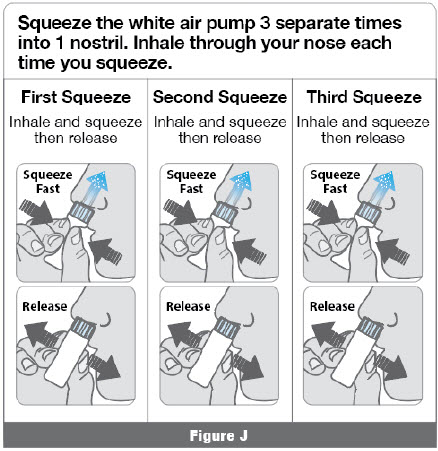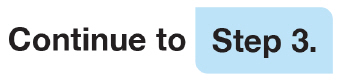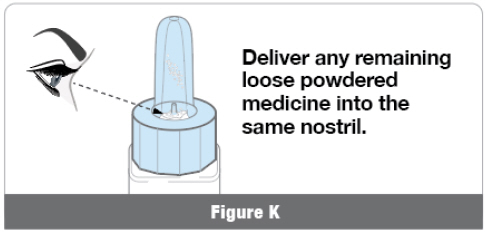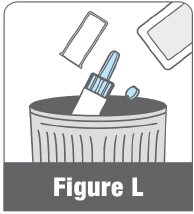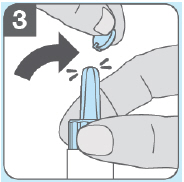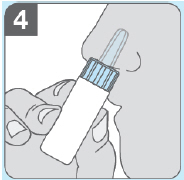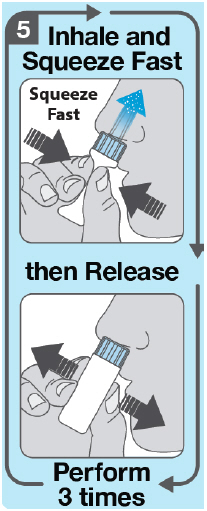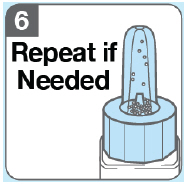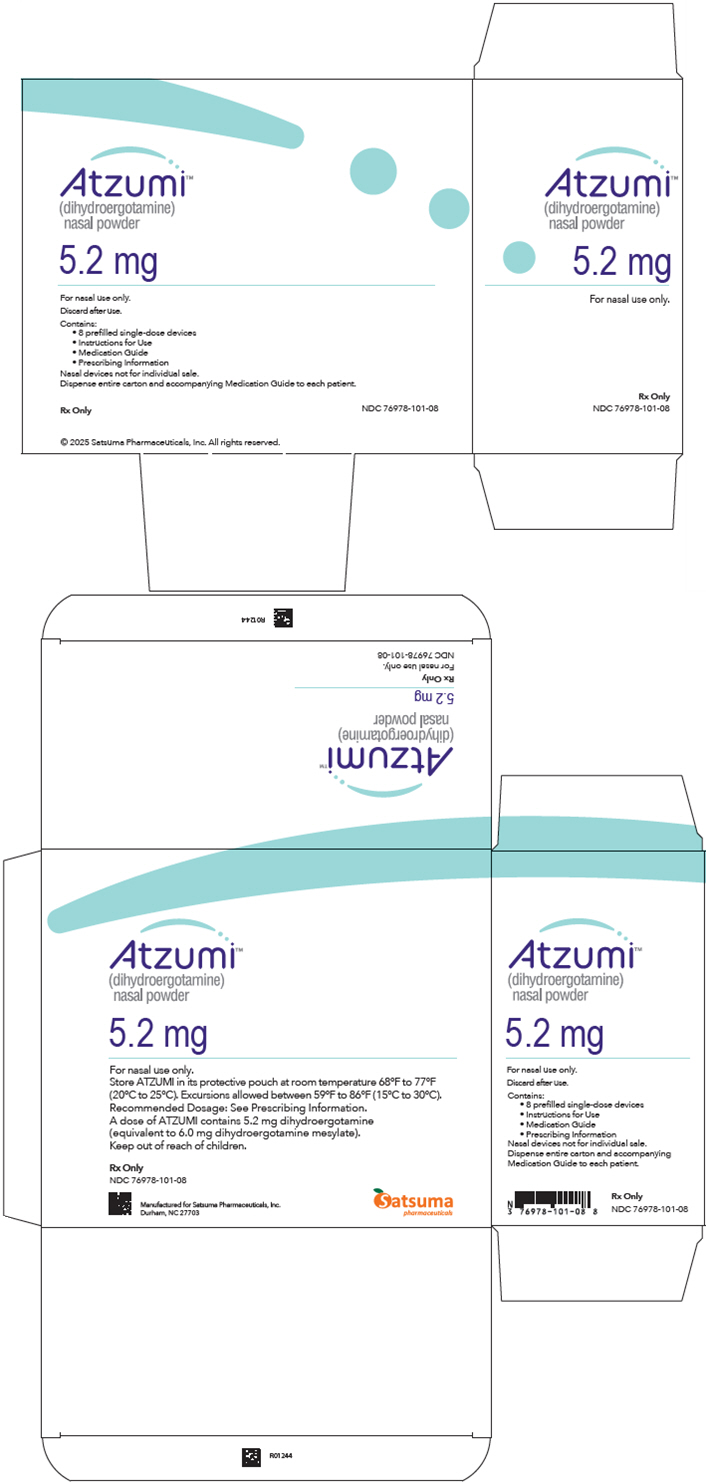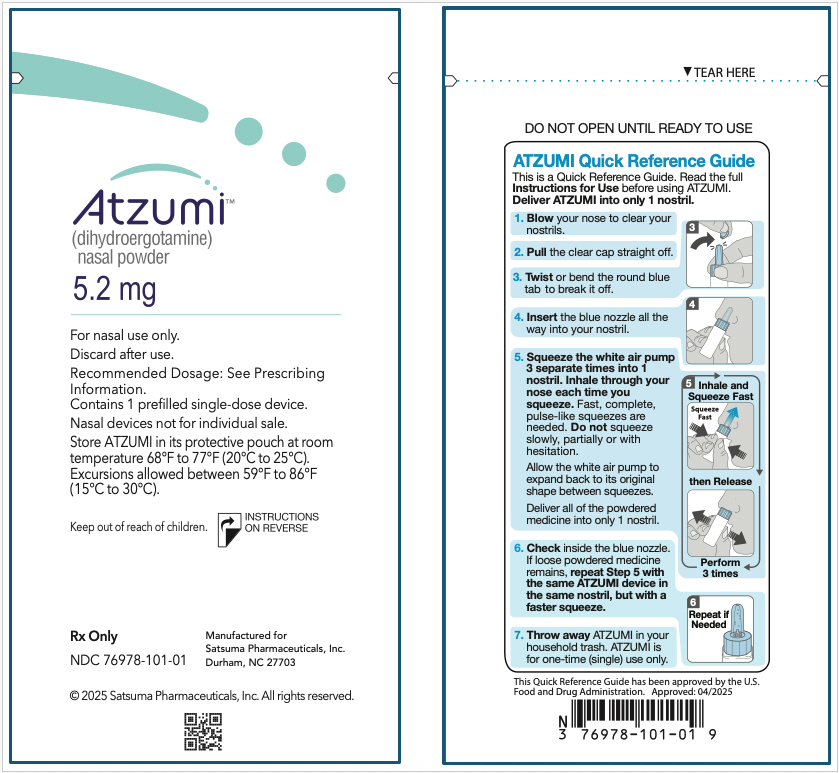 DRUG LABEL: ATZUMI
NDC: 76978-101 | Form: POWDER
Manufacturer: Satsuma Pharmaceuticals, Inc.
Category: prescription | Type: HUMAN PRESCRIPTION DRUG LABEL
Date: 20250508

ACTIVE INGREDIENTS: DIHYDROERGOTAMINE MESYLATE 5.2 mg/1 1
INACTIVE INGREDIENTS: MICROCRYSTALLINE CELLULOSE; HYPROMELLOSE, UNSPECIFIED; MANNITOL

HIGHLIGHTS OF PRESCRIBING INFORMATION

These highlights do not include all the information needed to use ATZUMI safely and effectively. See full prescribing information for ATZUMI.
ATZUMI™ (dihydroergotamine) nasal powder
Initial U.S. Approval: 1946

WARNING: PERIPHERAL ISCHEMIA FOLLOWING COADMINISTRATION WITH STRONG CYP3A4 INHIBITORS

See full prescribing information for complete boxed warning.

Serious and/or life-threatening peripheral ischemia has been associated with the coadministration of dihydroergotamine with strong CYP3A4 inhibitors. Because CYP3A4 inhibition elevates the serum levels of dihydroergotamine, the risk for vasospasm leading to cerebral ischemia and/or ischemia of the extremities is increased. Hence, concomitant use of ATZUMI with strong CYP3A4 inhibitors is contraindicated. (4, 5.1, 7.1)

1 INDICATIONS AND USAGE

ATZUMI is an ergotamine derivative indicated for the acute treatment of migraine with or without aura in adults. (1)

Limitations of Use

ATZUMI is not indicated for the preventive treatment of migraine or for the management of hemiplegic migraine or migraine with brainstem aura. (1)

2 DOSAGE AND ADMINISTRATION

- ATZUMI is for nasal administration only. (2.1)
- The recommended dose of ATZUMI is 5.2 mg, the contents of one nasal device, administered into one nostril. (2.1)
- To administer a dose, the white air pump of the ATZUMI device must be squeezed three separate times into one nostril. (2.1)
- The dose may be repeated, if needed, a minimum of 1 hour after the first dose. The maximum dose in a 24-hour period is 10.4 mg (two doses of ATZUMI 5.2 mg). (2.1)
- The safety of taking more than 4 doses within a 7-day period or 12 doses within a 30-day period has not been established. (2.1)
- Prior to initiation, a cardiovascular evaluation is recommended. (2.2)

3 DOSAGE FORMS AND STRENGTHS

Nasal powder: 5.2 mg (3)

4 CONTRAINDICATIONS

- Concomitant use of strong CYP3A4 inhibitors. (4)
- Ischemic heart disease or coronary artery vasospasm (4)
- Uncontrolled hypertension, peripheral arterial diseases, sepsis, following vascular surgery, or severe hepatic or renal impairment (4)
- Hypersensitivity to ergot alkaloids (4)
- Concomitant use of other 5-HT1 agonists or ergotamine-containing or ergot-type medications within 24 hours (4)
- Concomitant use of peripheral and central vasoconstrictors (4)

5 WARNINGS AND PRECAUTIONS

- Myocardial Ischemia and/or Infarction, Other Cardiac Adverse Reactions, and Fatalities: In patients with risk factors predictive of coronary artery disease, consider first dose administration under medical supervision with electrocardiogram. (5.2)
- Cerebrovascular Adverse Reactions and Fatalities: Cerebral hemorrhage, subarachnoid hemorrhage, and stroke have been reported; discontinue ATZUMI if suspected. (5.3)
- Other Vasospasm Related Adverse Reactions: ATZUMI may cause vasospasm or elevation in blood pressure. Discontinue if signs or symptoms of vasoconstriction develop. (5.4, 5.5)
- Medication Overuse Headache: Detoxification may be necessary. (5.6)
- Preterm Labor: Advise pregnant women of the risk. (5.7, 8.1)
- Fibrotic Complications: Pleural and retroperitoneal fibrosis have been reported following prolonged daily use of dihydroergotamine. Administration of ATZUMI should not exceed the dosing guidelines or be used for chronic daily administration. (5.8)
- Local Irritation: If severe local irritation occurs for no other attributable reason, suspend ATZUMI until resolution. (5.9)

6 ADVERSE REACTIONS

Most common adverse reactions (incidence > 1%) were rhinitis, nausea, altered sense of taste, application site reactions, dizziness, vomiting, somnolence, pharyngitis, and diarrhea. (6.1)

To report SUSPECTED ADVERSE REACTIONS, contact Satsuma Pharmaceuticals, Inc. at toll-free phone # 1-888-273-2480 or FDA at 1-800-FDA-1088 or www.fda.gov/medwatch.

7 DRUG INTERACTIONS

- Beta Blockers/Nicotine: May potentiate/provoke vasoconstriction. (7.3, 7.5)
- Selective Serotonin Reuptake Inhibitors: Weakness, hyperreflexia, and incoordination may occur with coadministration. (7.6)

8 USE IN SPECIFIC POPULATIONS

- Pregnancy: Based on animal data, may cause fetal harm. (8.1)
- Lactation: Advise not to use during breastfeeding. (8.2)

FULL PRESCRIBING INFORMATION

WARNING: PERIPHERAL ISCHEMIA FOLLOWING COADMINISTRATION WITH STRONG CYP3A4 INHIBITORS

Serious and/or life-threatening peripheral ischemia has been associated with the coadministration of dihydroergotamine with strong CYP3A4 inhibitors. Because CYP3A4 inhibition elevates the serum levels of dihydroergotamine, the risk for vasospasm leading to cerebral ischemia and/or ischemia of the extremities is increased. Hence, concomitant use of ATZUMI with strong CYP3A4 inhibitors is contraindicated [see Contraindications (4), Warnings and Precautions (5.1), and Drug Interactions (7.1)].

1 INDICATIONS AND USAGE

ATZUMI is indicated for the acute treatment of migraine with or without aura in adults.

Limitations of Use

ATZUMI is not indicated for the preventive treatment of migraine.

ATZUMI is not indicated for the management of hemiplegic migraine or migraine with brainstem aura.

2 DOSAGE AND ADMINISTRATION

2.1 Dosing Information

ATZUMI is for nasal administration only.

The recommended dose of ATZUMI is 5.2 mg (the contents of one nasal device) and is administered as a powdered medicine into one nostril [see Dosage and Administration (2.3)].

The dose may be repeated, if needed, a minimum of 1 hour after the first dose. The maximum dose in a 24-hour period is 10.4 mg (two doses of ATZUMI 5.2 mg). The safety of taking more than 4 doses in a 7-day period or 12 doses within a 30-day period has not been established.

2.2 Assessment Prior to First Dose

Prior to initiation of ATZUMI, a cardiovascular evaluation is recommended [see Warnings and Precautions (5.2)]. For patients with risk factors predictive of coronary artery disease who are determined to have a satisfactory cardiovascular evaluation, it is strongly recommended that administration of the first dose of ATZUMI take place in the setting of an equipped healthcare facility.

2.3 Administration Instructions

- Priming is not required.
- To administer a dose of ATZUMI, remove the round blue tab from the blue nozzle, and insert the blue nozzle into one nostril. Squeeze the white air pump 3 separate times into 1 nostril while inhaling. Allow the white air pump to expand back to its original shape between squeezes [see Instructions for Use].
- Fast, complete, pulse-like squeezes are needed to deliver the complete dose. Do not squeeze slowly, partially or with any hesitation.

3 DOSAGE FORMS AND STRENGTHS

Nasal Powder: 5.2 mg dihydroergotamine as a white powder in a single-dose nasal device.

4 CONTRAINDICATIONS

ATZUMI is contraindicated in patients:

- with concomitant use of strong CYP3A4 inhibitors [see Warnings and Precautions (5.1) and Drug Interactions (7.1)]
- with ischemic heart disease (e.g., angina pectoris, history of myocardial infarction, or documented silent ischemia) or patients who have clinical symptoms or findings consistent with coronary artery vasospasm, including Prinzmetal's variant angina [see Warnings and Precautions (5.4)]
- with uncontrolled hypertension [see Warnings and Precautions (5.5)]
- with peripheral arterial disease
- with sepsis
- following vascular surgery
- with severe hepatic impairment
- with severe renal impairment
- with known hypersensitivity to ergot alkaloids
- with recent use (i.e., within 24 hours) of other 5-HT1 agonists or ergotamine-containing or ergot-type medications [see Drug Interactions (7.2)]
- with concomitant use of peripheral and central vasoconstrictors because the combination may result in additive or synergistic elevation of blood pressure [see Warnings and Precautions (5.5)]

5 WARNINGS AND PRECAUTIONS

5.1 Peripheral Ischemia Following Coadministration with Strong CYP3A4 Inhibitors

Serious and/or life-threatening peripheral ischemia has been associated with the coadministration of dihydroergotamine with strong CYP3A4 inhibitors, including protease inhibitors, macrolide antibiotics, and antifungals. Because CYP3A4 inhibition elevates the serum levels of dihydroergotamine, the risk for vasospasm leading to cerebral ischemia and/or ischemia of the extremities is increased. Hence, concomitant use of ATZUMI with strong CYP3A4 inhibitors is contraindicated [see Contraindications (4) and Drug Interactions (7.1)].

5.2 Myocardial Ischemia and/or Infarction, Other Cardiac Adverse Reactions, and Fatalities

The potential for cardiac adverse reactions exists with ATZUMI treatment. Serious adverse cardiac events, including some that have been fatal, have occurred following use of dihydroergotamine. These events have included acute myocardial infarction, life-threatening disturbances of cardiac rhythm (e.g., ventricular tachycardia and ventricular fibrillation), coronary artery vasospasm, and transient myocardial ischemia.

Prior to initiation of ATZUMI, a cardiovascular evaluation is recommended to determine if the patient is free of coronary artery and ischemic myocardial disease or other significant underlying cardiovascular disease. If, during the cardiovascular evaluation, the patient's medical history (including risk factors), or electrocardiographic investigation, findings are consistent with coronary artery vasospasm or myocardial ischemia, ATZUMI should not be administered [see Contraindications (4)].

For patients with risk factors predictive of coronary artery disease (e.g., hypertension, hypercholesterolemia, smoker, obesity, diabetes, strong family history of coronary artery disease, females who are surgically or physiologically postmenopausal, or males who are over 40 years of age) who are determined to have a satisfactory cardiovascular evaluation, it is strongly recommended that administration of the first dose of ATZUMI take place in the setting of an equipped healthcare facility, unless the patient has previously received dihydroergotamine. During the interval immediately following the first use of ATZUMI, an electrocardiogram is recommended in those patients with risk factors because ischemia can occur in the absence of clinical symptoms.

5.3 Cerebrovascular Adverse Reactions and Fatalities

The potential for adverse cerebrovascular adverse reactions exists with ATZUMI treatment. Cerebral hemorrhage, subarachnoid hemorrhage, stroke, and other cerebrovascular events have been reported in patients treated with dihydroergotamine; and some have resulted in fatalities. In a number of cases, it appears possible that the cerebrovascular events were primary, the dihydroergotamine having been administered in the incorrect belief that the symptoms experienced were a consequence of migraine, when they were not. It should be noted that patients with migraine may be at increased risk of certain cerebrovascular events (e.g., stroke, hemorrhage, transient ischemic attack).

Discontinue ATZUMI if a cerebrovascular event is suspected.

5.4 Other Vasospasm Related Adverse Reactions

ATZUMI, like other ergot alkaloids, may cause vasospastic reactions other than coronary artery vasospasm. Myocardial, peripheral vascular, and colonic ischemia have been reported with dihydroergotamine.

Dihydroergotamine associated vasospastic phenomena may also cause muscle pains, numbness, coldness, pallor, and cyanosis of the digits. In patients with compromised circulation, persistent vasospasm may result in gangrene or death. ATZUMI should be discontinued immediately if signs or symptoms of vasoconstriction develop.

Patients who experience other symptoms or signs suggestive of decreased arterial flow, such as ischemic bowel syndrome or Raynaud's syndrome, following the use of any 5-HT1 agonist, including ATZUMI, should be evaluated by a healthcare provider.

5.5 Increase in Blood Pressure

Significant elevation in blood pressure has been reported on rare occasions in patients with and without a history of hypertension treated with dihydroergotamine. ATZUMI is contraindicated in patients with uncontrolled hypertension [see Contraindications (4)].

An 18% increase in mean pulmonary artery pressure was seen following dosing with another 5-HT1 agonist in a study evaluating subjects undergoing cardiac catheterization.

5.6 Medication Overuse Headache

Overuse of acute migraine drugs (e.g., ergotamines, triptans, opioids, or a combination of these drugs for 10 or more days per month) may lead to exacerbation of headache (i.e., medication overuse headache). Medication overuse headache may present as migraine-like daily headaches or as a marked increase in frequency of migraine attacks. Detoxification of patients including withdrawal of the overused drugs and treatment of withdrawal symptoms (which often includes a transient worsening of headache) may be necessary.

5.7 Preterm Labor

Based on the mechanism of action of dihydroergotamine and findings from the published literature, ATZUMI may cause preterm labor. Avoid use of ATZUMI during pregnancy [see Use in Specific Populations (8.1) and Clinical Pharmacology (12.2)].

5.8 Fibrotic Complications

The potential for fibrotic complications exists with ATZUMI treatment. There have been reports of pleural and retroperitoneal fibrosis in patients following prolonged daily use of dihydroergotamine . Rarely, prolonged daily use of other ergot alkaloid drugs has been associated with cardiac valvular fibrosis. Rare cases have also been reported in association with the use of dihydroergotamine; however, in those cases, patients also received drugs known to be associated with cardiac valvular fibrosis.

Administration of ATZUMI should not exceed the dosing guidelines and should not be used for chronic daily administration [see Dosage and Administration (2.1)].

5.9 Local Irritation

Local irritative symptoms were reported in 29% of patients treated with at least one dose of ATZUMI in an open-labeled trial, which allowed repeated use of ATZUMI up to 12 months. The common local irritative symptoms (at least 1% of patients) were nasal discomfort (11%), altered taste (8%), nasal congestion (5%), nasopharyngitis (5%), rhinorrhea (4%), cough (3%), nasal pain (3%), epistaxis (2%), sneezing (2%), nasal pruritus (1%), and increased lacrimation (1%). If a severe local irritation event occurs for no other attributable reasons, avoid further use of ATZUMI until the event resolves. Monitor patients for severe recurrent local irritation.

Nasal tissue in animals treated with dihydroergotamine mesylate daily showed mild mucosal irritation characterized by mucous cell and transitional cell hyperplasia and squamous cell metaplasia. Changes in rat nasal mucosa at 64 weeks were less severe than at 13 weeks. Local effects on respiratory tissue after chronic intranasal dosing in animals have not been evaluated.

6 ADVERSE REACTIONS

The following clinically significant adverse reactions are described elsewhere in the labeling:

- Peripheral Ischemia Following Coadministration with Strong CYP3A4 Inhibitors [see Boxed Warning and Warnings and Precautions (5.1)]
- Myocardial Ischemia and/or Infarction, Other Adverse Cardiac Events, and Fatalities [see Warnings and Precautions (5.2)]
- Cerebrovascular Adverse Reactions and Fatalities [see Warnings and Precautions (5.3)]
- Other Vasospasm Related Adverse Reactions [see Warnings and Precautions (5.4)]
- Increase in Blood Pressure [see Warnings and Precautions (5.5)]
- Medication Overuse Headache [see Warnings and Precautions (5.6)]
- Preterm Labor [see Warnings and Precautions (5.7)]
- Fibrotic Complications [see Warnings and Precautions (5.8)]
- Local Irritation [see Warnings and Precautions (5.9)]

6.1 Clinical Trials Experience

Because clinical trials are conducted under widely varying conditions, adverse reaction rates observed in the clinical trials of a drug cannot be directly compared to rates in the clinical trials of another drug and may not reflect the rates observed in practice.

The studies described below were conducted with dihydroergotamine mesylate nasal spray; adverse reactions with ATZUMI nasal powder are expected to be similar to adverse reactions with dihydroergotamine mesylate nasal spray.

Adverse Reactions in Placebo-Controlled Trials with Dihydroergotamine Mesylate Nasal Spray [see Clinical Studies (14)]

Of the 1,796 patients and subjects treated with dihydroergotamine mesylate nasal spray doses 2 mg or less in U.S. and foreign clinical studies, 26 (1.4%) discontinued because of adverse events. The adverse events associated with discontinuation were, in decreasing order of frequency: rhinitis (13), dizziness (2), facial edema (2), and one patient each due to cold sweats, accidental trauma, depression, elective surgery, somnolence, allergy, vomiting, hypotension, and paraesthesia.

Table 1 summarizes the incidence rates of adverse reactions reported by at least 1% of patients who received dihydroergotamine mesylate nasal spray for the treatment of migraine during placebo-controlled, double-blind clinical studies and were more frequent than in those patients receiving placebo. The most commonly reported adverse reactions (greater than 1% of patients who received dihydroergotamine mesylate nasal spray) were rhinitis, nausea, altered sense of taste, application site reactions, dizziness, vomiting, somnolence, pharyngitis, and diarrhea. In most instances these events were transient and self-limited and did not result in patient discontinuation from a study.

Table 1 Adverse Reactions Reported by at Least 1% of the Dihydroergotamine Mesylate Nasal Spray Treated Patients and Occurred more Frequently than in the Placebo-Group in the Migraine Placebo-Controlled Trials
 | Dihydroergotamine Mesylate Nasal Spray N=597 % | Placebo N=631 %
Respiratory System
Rhinitis | 26 | 7
Pharyngitis | 3 | 1
Gastrointestinal System
Nausea | 10 | 4
Vomiting | 4 | 1
Diarrhea | 2 | <1
Special Senses, Other
Altered Sense of Taste | 8 | 1
Application Site
Application Site Reaction | 6 | 2
Central and Peripheral Nervous System
Dizziness | 4 | 2
Somnolence | 3 | 2
Body as a Whole, General
Hot Flashes | 1 | <1
Asthenia | 1 | 0
Musculoskeletal System
Stiffness | 1 | <1

Adverse Reactions in Studies with ATZUMI

An open-label study in adults was conducted to evaluate the safety and tolerability of ATZUMI, with repeated use of ATZUMI over the course of 6 to 12 months. A total of 344 patients with migraine received at least one dose of ATZUMI. One hundred and eighty-eight patients treated on average at least two migraines per month for at least 6 months, and 86 patients treated at least two migraines per month for at least one year. Of the patients who received at least one dose of ATZUMI, 99 (29%) experienced local irritative symptoms. Of these, the most common local irritative symptoms (at least 5% of patients) were nasal discomfort, altered taste, nasal congestion, and nasopharyngitis [see Warnings and Precautions (5.9)]. The most common adverse reaction resulting in discontinuation in the long-term safety study was nasal discomfort (1.5%).

6.2 Postmarketing Experience

The following adverse reactions have been identified during postapproval use of dihydroergotamine. Because these reactions are reported voluntarily from a population of uncertain size, it is not always possible to reliably estimate their frequency or establish a causal relationship to drug exposure:

Vasospasm, paresthesia, hypertension, dizziness, anxiety, dyspnea, headache, flushing, diarrhea, rash, increased sweating, and pleural and retroperitoneal fibrosis after long-term use of dihydroergotamine. Cases of myocardial infarction and stroke have been reported following the use of dihydroergotamine [see Warnings and Precautions (5.2)].

7 DRUG INTERACTIONS

7.1 CYP3A4 Inhibitors

There have been rare reports of serious adverse events in connection with the coadministration of intravenous administration of dihydroergotamine and strong CYP3A4 inhibitors, resulting in vasospasm that led to cerebral ischemia and/or ischemia of the extremities [see Warnings and Precautions (5.1)]. The use of strong CYP3A4 inhibitors with ATZUMI is contraindicated [see Contraindications (4)]. Administer moderate CYP3A4 inhibitors with caution.

7.2 Triptans

Triptans (serotonin [5-HT] 1B/1D receptor agonists) have been reported to cause coronary artery vasospasm, and its effects could be additive with ATZUMI. Therefore, triptans and ATZUMI should not be taken within 24 hours of each other [see Contraindications (4)].

7.3 Beta Blockers

There have been reports that propranolol may potentiate the vasoconstrictive action of ergotamine by blocking the vasodilating property of epinephrine.

7.4 Vasoconstrictors

ATZUMI is contraindicated for use with peripheral and central vasoconstrictors because the combination may cause synergistic elevation of blood pressure [see Warnings and Precautions (5.5)].

7.5 Nicotine

Nicotine may provoke vasoconstriction in some patients, predisposing to a greater ischemic response to ergot therapy [see Warnings and Precautions (5.2, 5.4)].

7.6 Selective Serotonin Reuptake Inhibitors

Weakness, hyperreflexia, and incoordination have been reported rarely when 5-HT1 agonists have been co-administered with selective serotonin reuptake inhibitors (e.g., fluoxetine, fluvoxamine, paroxetine, sertraline).

8 USE IN SPECIFIC POPULATIONS

8.1 Pregnancy

Risk Summary

Available data from published literature indicate an increased risk of preterm delivery with dihydroergotamine, the active moiety in ATZUMI, use during pregnancy. Avoid use of ATZUMI during pregnancy [see Warnings and Precautions (5.7)]. Data collected over decades have shown no increased risk of major birth defects or miscarriage with the use of dihydroergotamine during pregnancy.

In animal reproduction studies, adverse effects on development were observed following intranasal administration of dihydroergotamine mesylate during pregnancy (decreased fetal body weight and/or skeletal ossification) in rats and rabbits or during pregnancy and lactation in rats (decreased body weight and impaired reproductive function in the offspring) at doses that were not associated with maternal toxicity (see Data).

All pregnancies have a background risk of birth defect, loss, or other adverse outcomes. In the U.S. general population, the estimated background risk of major birth defects and miscarriages in clinically recognized pregnancies is 2% to 4% and 15% to 20%, respectively. The estimated rate of major birth defects (2.2% to 2.9%) and miscarriage (17%) among deliveries to women with migraine are similar to rates reported in women without migraine.

Clinical Considerations

Disease-Associated Maternal and/or Embryo/Fetal Risk

Published data have suggested that women with migraine may be at increased risk of preeclampsia and gestational hypertension during pregnancy.

Data

Animal Data

Intranasal administration of dihydroergotamine mesylate to pregnant rats throughout the period of organogenesis resulted in decreased fetal body weight and/or skeletal ossification at doses of 0.16 mg/day and greater. A no-effect level for adverse effects on embryofetal development was not identified in rats.

Intranasal administration of dihydroergotamine mesylate to pregnant rabbits throughout organogenesis resulted in decreased skeletal ossification at 3.6 mg/day. The no-effect dose for adverse effects on embryofetal development in rabbits was 1.2 mg/day.

Intranasal administration of dihydroergotamine mesylate to female rats throughout pregnancy and lactation resulted in decreased body weight and impaired reproductive function (decreased mating indices) in the offspring at doses of 0.16 mg/day or greater. A no-effect dose for adverse effects on pre- and postnatal development in rats was not established. Effects on offspring development occurred at doses below those that produced evidence of significant maternal toxicity in these studies.

Dihydroergotamine-induced intrauterine growth retardation has been attributed to reduced uteroplacental blood flow resulting from prolonged vasoconstriction of the uterine vessels and/or increased myometrial tone.

8.2 Lactation

Risk Summary

There are no data on the presence of dihydroergotamine in human milk; however, ergotamine, a related drug, is present in human milk. There are reports of diarrhea, vomiting, weak pulse, and unstable blood pressure in breastfed infants exposed to ergotamine. ATZUMI may reduce milk supply because it may decrease prolactin levels. Because of the potential for reduced milk supply and serious adverse events in the breastfed infant, including diarrhea, vomiting, weak pulse, and unstable blood pressure, advise patients not to breastfeed during treatment with ATZUMI and for 3 days after the last dose. Breast milk supply during this time should be pumped and discarded.

8.4 Pediatric Use

The safety and effectiveness of ATZUMI have not been established in pediatric patients.

8.5 Geriatric Use

Clinical studies of ATZUMI and other dihydroergotamine products did not include sufficient numbers of subjects aged 65 and older to determine whether they respond differently from younger subjects. In general, dose selection for an elderly patient should be cautious, usually starting at the low end of the dosing range, reflecting the greater frequency of decreased hepatic, renal, or cardiac function and of concomitant disease or other drug therapy.

9 DRUG ABUSE AND DEPENDENCE

9.1 Controlled Substance

ATZUMI contains dihydroergotamine (as the mesylate salt), which is not a controlled substance.

9.2 Abuse

Abuse is the intentional, non-therapeutic use of a drug, even once, for its desirable psychological or physiological effects. Currently available data have not demonstrated drug abuse with dihydroergotamine. However, cases of drug abuse in patients on other forms of ergot therapy have been reported.

9.3 Dependence

Physical dependence is a state that develops as a result of physiological adaptation in response to repeated drug use, manifested by withdrawal signs and symptoms after abrupt discontinuation or a significant dose reduction of a drug. Currently available data have not demonstrated physical or psychological dependence with dihydroergotamine. However, cases of psychological dependence in patients on other forms of ergot therapy have been reported.

10 OVERDOSAGE

10.1 Symptoms

Excessive doses of dihydroergotamine may result in peripheral signs and symptoms of ergotism. In general, the symptoms of an acute ATZUMI overdose may be similar to those of an ergotamine overdose, although there may be less pronounced nausea and vomiting with ATZUMI. The symptoms of an ergotamine overdose include the following: numbness, tingling, pain, and cyanosis of the extremities associated with diminished or absent peripheral pulses; respiratory depression; an increase and/or decrease in blood pressure, usually in that order; confusion, delirium, convulsions, and coma; and/or some degree of nausea, vomiting, and abdominal pain.

In laboratory animals, dihydroergotamine mesylate was lethal when given at intravenous doses of 44 mg/kg in mice, 130 mg/kg in rats, and 37 mg/kg in rabbits.

10.2 Treatment

Treatment of an overdose of ATZUMI should consist of discontinuation of the drug, general supportive measures including monitoring of vital signs, and observation of the clinical status of the patient for at least 24 hours, or while symptoms or signs persist. Consider contacting the Poison Help line (1-800-222-1222) or a medical toxicologist for additional overdose management recommendations.

11 DESCRIPTION

ATZUMI contains dihydroergotamine, an ergotamine derivative, as the mesylate salt. Dihydroergotamine mesylate is a white or almost white crystalline powder. It is slightly soluble in water and chloroform and sparingly soluble in methanol. The chemical designation for dihydroergotamine mesylate is (6aR,9R,10aR)-N-[(2R,5S,10aS,10bS)-5-benzyl-10b-hydroxy-2-methyl-3,6-dioxo-octahydro-8H-oxazolo[3,2-α]pyrrolo[2,1-c]pyrazin-2-yl]-7-methyl- 4,6,6a,7,8,9,10,10a-octahydroindolo[4,3-fg]quinoline-9-carboxamide methanesulphonate. The empirical formula is C33H37N5O5 ∙ CH4O3S. The molecular weight is 679.80, and it has the following structure:

ATZUMI contains dihydroergotamine 5.2 mg (equivalent to 6.0 mg dihydroergotamine mesylate).

ATZUMI nasal powder is a drug-device combination product consisting of a powder prefilled in a single-dose delivery device for nasal administration into one nostril. ATZUMI does not need to be assembled or primed before use. Inactive ingredients are hypromellose, mannitol, and microcrystalline cellulose.

12 CLINICAL PHARMACOLOGY

12.1 Mechanism of Action

Dihydroergotamine binds with high affinity to 5-HT1Dα and 5-HT1Dβ receptors.

The therapeutic activity of dihydroergotamine in migraine is generally attributed to the agonist effects at 5-HT1D receptors.

12.2 Pharmacodynamics

Significant elevation in blood pressure has been reported in patients treated with dihydroergotamine with and without a history of hypertension [see Warnings and Precautions (5.5)].

Dihydroergotamine possesses oxytocic properties [see Warnings and Precautions (5.7)].

12.3 Pharmacokinetics

Absorption

Following ATZUMI administration, the mean maximum plasma concentration was 2.1 ng/mL, and the median time from dosing to maximum plasma concentration was approximately 0.5 hours.

Distribution

Dihydroergotamine is 93% plasma protein bound. The apparent steady-state volume of distribution is approximately 800 liters.

Elimination

The mean apparent half-life of dihydroergotamine following nasal administration of ATZUMI in healthy subjects is approximately 13 hours.

Metabolism

Four dihydroergotamine mesylate metabolites have been identified in human plasma following oral administration. The major metabolite, 8'-β-hydroxydihydroergotamine, exhibits affinity equivalent to its parent for adrenergic and 5-HT1 receptors and demonstrates equivalent potency in several venoconstrictor activity models, in vivo and in vitro. The other metabolites, (i.e., dihydrolysergic acid, dihydrolysergic amide) and a metabolite formed by oxidative opening of the proline ring are of minor importance.

Following nasal administration of ATZUMI, the 8'-β-hydroxydihydroergotamine metabolite plasma AUC was approximately 16% of the plasma AUC of dihydroergotamine, and the mean Cmax (5.7% of parent) was below the minimal concentrations required for receptor binding for adrenergic and 5-HT1 receptors.

Excretion

The major excretory route of dihydroergotamine is via the bile in the feces. The total body clearance following ATZUMI administration is 1.5 L/min which reflects mainly hepatic clearance. The renal clearance (0.1 L/min) is unaffected by the route of dihydroergotamine administration based on other dihydroergotamine products.

Specific Populations

No studies have been conducted on the effect of renal or hepatic impairment, gender, race, ethnicity, or pregnancy on dihydroergotamine pharmacokinetics [see Contraindications (4), Use in Specific Populations (8.1)].

Drug Interaction Studies

CYP3A4 Inhibitors

In a drug interaction study, administration of ATZUMI with itraconazole increased dihydroergotamine plasma exposure by 14% for Cmax and 19% for AUC while the plasma exposures (Cmax and AUC0-inf) of 8'-β-hydroxy dihydroergotamine (8'-OH-DHE, active metabolite) were increased by approximately 4-fold and 3-fold, respectively [see Contraindications (4), Warnings and Precautions (5.1), Drug Interactions (7.1)].

Other Drugs

The pharmacokinetics of dihydroergotamine did not appear to be significantly affected by the concomitant use of a local vasoconstrictor.

Multiple oral doses of the β-adrenoceptor antagonist propranolol, used for preventive treatment of migraine, had no significant influence on the Cmax, Tmax or AUC of dihydroergotamine doses up to 4 mg [see Drug Interactions (7.3)].

The effect of oral contraceptives on the pharmacokinetics of dihydroergotamine has not been studied.

13 NONCLINICAL TOXICOLOGY

13.1 Carcinogenesis, Mutagenesis, Impairment of Fertility

Carcinogenesis

In a 2-year mouse carcinogenicity study, subcutaneous administration of dihydroergotamine mesylate (0, 0.5, 1.5, or 5 mg/kg/day) resulted in an increased incidence of fibrosarcoma at the injection sites in males and females at the high dose.

In a 2-year rat carcinogenicity study, intranasal administration of dihydroergotamine mesylate (0, 0.4, 0.8, or 1.6 mg/day for 13 weeks, followed by 0, 0.08, 0.24, or 0.8 mg/day for the remainder of the study) did not result in an increase in tumors.

Mutagenesis

Dihydroergotamine mesylate was negative in an in vitro mutagenicity (Ames) assay and positive in in vitro chromosomal aberration (V79 Chinese hamster cell assay with metabolic activation, and human peripheral blood lymphocyte) assays. Dihydroergotamine was negative in in vivo micronucleus assays in mouse and hamster.

Impairment of Fertility

Intranasal administration of dihydroergotamine to rats at doses up to 1.6 mg/day was not associated with adverse effects on fertility.

14 CLINICAL STUDIES

The efficacy of ATZUMI for the acute treatment of migraine with or without aura in adults was based on the relative bioavailability of ATZUMI nasal powder compared to dihydroergotamine mesylate nasal spray.

The clinical trials described below were conducted using dihydroergotamine mesylate nasal spray.

The efficacy of dihydroergotamine mesylate nasal spray for the acute treatment of migraine headaches was evaluated in four randomized, double-blind, placebo controlled studies in the U.S. The patient population for the trials was predominantly female (87%) and Caucasian (95%) with a mean age of 39 years (range 18 to 65 years). Patients treated a single moderate to severe migraine headache with a single dose of study medication and assessed pain severity over the 24 hours following treatment. Headache response was determined 0.5, 1, 2, 3 and 4 hours after dosing and was defined as a reduction in headache severity to mild or no pain. In studies 1 and 2, a four-point pain intensity scale was utilized; in studies 3 and 4, a five-point scale was used to record pain response. Although rescue medication was allowed in all four studies, patients were instructed not to use them during the four hour observation period. In studies 3 and 4, a total dose of 2 mg was compared to placebo. In studies 1 and 2, doses of 2 and 3 mg were evaluated, and showed no advantage of the higher dose for a single treatment. In all studies, patients received a regimen consisting of 0.5 mg in each nostril, repeated in 15 minutes (and again in another 15 minutes for the 3 mg dose in studies 1 and 2).

The percentage of patients achieving headache response 4 hours after treatment was significantly greater in patients receiving 2 mg doses of dihydroergotamine mesylate nasal spray compared to those receiving placebo in 3 of the 4 studies (see Table 2 and Table 3 and Figure 1 and Figure 2).

Table 2 Studies 1 and 2: Percentage of Patients with Headache Response [Headache response was defined as a reduction in headache severity to mild or no pain. Headache response was based on pain intensity as interpreted by the patient using a four-point pain intensity scale.] 2 and 4 Hours Following a Single Treatment of Study Medication (Dihydroergotamine Mesylate Nasal Spray or Placebo)
 |  | N | 2 hours | 4 hours
Study 1 | Dihydroergotamine mesylate nasal spray | 105 | 61% [p value < 0.001] | 70%
Study 1 | Placebo | 98 | 23% | 28%
 | Difference from Placebo |  | 37% | 42%
Study 2 | Dihydroergotamine mesylate nasal spray | 103 | 47% | 56% [p value < 0.01]
Study 2 | Placebo | 102 | 33% | 35%
 | Difference from Placebo |  | 14% | 21%

Table 3 Studies 3 and 4: Percentage of Patients with Headache Response [Headache response was defined as a reduction in headache severity to mild or no pain. Headache response was evaluated on a five-point scale that included pain response.] 2 and 4 Hours Following a Single Treatment of Study Medication (Dihydroergotamine Mesylate Nasal Spray or Placebo)
 |  | N | 2 hours | 4 hours
Study 3 | Dihydroergotamine mesylate nasal spray | 50 | 32% | 48% [p value < 0.01]
Study 3 | Placebo | 50 | 20% | 22%
 | Difference from Placebo |  | 12% | 26%
Study 4 | Dihydroergotamine mesylate nasal spray | 47 | 30% | 47%
Study 4 | Placebo | 50 | 20% | 30%
 | Difference from Placebo |  | 10% | 17%

The Kaplan-Meier plots below (Figure 1 and Figure 2) provides an estimate of the probability that a patient will have responded to a single 2 mg dose of dihydroergotamine mesylate nasal spray as a function of the time elapsed since initiation of treatment.

Figure 1 Estimated Probability of a Patient Responding During the Four Hours Following a Single 2 mg Dose of Dihydroergotamine Mesylate Nasal Spray as a Function of the Time Elapsed Since Initiation of Treatment [The figure shows the probability over time of obtaining a response following treatment with dihydroergotamine mesylate nasal spray. Headache response was based on pain intensity as interpreted by the patient using a four-point pain intensity scale. Patients not achieving response within 4 hours were censored to 4 hours.]

Figure 2 Estimated Probability of a Patient Responding to Dihydroergotamine Mesylate Nasal Spray During the Four Hours Following Dosing [The figure shows the probability over time of obtaining a response following treatment with dihydroergotamine mesylate nasal spray. Headache response was evaluated on a five-point scale that included pain response. Patients not achieving response within 4 hours were censored to 4 hours.]

For patients with migraine-associated nausea, photophobia, and phonophobia at baseline, there was a lower incidence of these symptoms at 2 and 4 hours following administration of dihydroergotamine mesylate nasal spray compared to placebo.

Patients were not allowed to use additional treatments for 8 hours prior to study medication dosing and during the 4-hour observation period following study treatment. Following the 4-hour observation period, patients were allowed to use additional treatments. For all studies, the estimated probability of patients using additional treatments for their migraines over the 24 hours following the single 2 mg dose of study treatment is summarized in Figure 3 below.

Figure 3 Estimated Probability of a Patient Using Additional Treatments for Migraine Over the 24 Hours Following Either Dihydroergotamine Mesylate Nasal Spray 2 mg (or Placebo) [Kaplan-Meier plot based on data obtained from all studies with patients not using additional treatments censored to 24 hours. All patients received a single treatment of study medication for their migraine attack. The plot also includes patients who had no response to the initial dose.]

Neither age nor sex appear to affect the patient's response to dihydroergotamine mesylate nasal spray. The racial distribution of patients was insufficient to determine the effect of race on the efficacy of dihydroergotamine mesylate nasal spray.

16 HOW SUPPLIED/STORAGE AND HANDLING

16.1 How Supplied

ATZUMI (dihydroergotamine) nasal powder is supplied in a single-dose nasal device with white powder containing 5.2 mg of dihydroergotamine. ATZUMI is available in a carton of 8 nasal devices each individually packaged in a protective foil pouch (NDC 76978-101-08).

16.2 Storage and Handling

Store ATZUMI at controlled room temperature, 20°C to 25°C (68°F to 77°F), with excursions allowed between 15°C to 30°C (59°F to 86°F).

Store ATZUMI in its protective foil pouch until ready to use.

17 PATIENT COUNSELING INFORMATION

Advise the patient to read the FDA-approved patient labeling (Medication Guide and Instructions for Use).

Serious and/or Life-Threatening Reactions with Coadministration of CYP3A4 Inhibitors

Inform patients that serious and/or life-threatening peripheral ischemia (cerebral ischemia and/or ischemia of the extremities) has been associated with the coadministration of dihydroergotamine and strong CYP3A4 inhibitors, such as macrolide antibiotics and protease inhibitors [see Contraindications (4), Warnings and Precautions (5.1), and Drug Interactions (7.1)].

Myocardial Ischemia and/or Infarction, Other Cardiac Events, Cerebrovascular Events, and Fatalities

Inform patients of the risk for serious cardiac, cerebrovascular, and other vasospasm related events. Advise patients to notify their healthcare provider if they develop any risk factors or symptoms while taking ATZUMI. Inform patients that nicotine may provoke vasoconstriction predisposing to a greater ischemic response [see Warnings and Precautions (5.2, 5.3, 5.4)].

Increase in Blood Pressure

Inform patients of the risk for significant elevation in blood pressure [see Warnings and Precautions (5.5)].

Medication Overuse Headache

Inform patients that use of drugs to treat migraine attacks for 10 or more days per month may lead to an exacerbation of headache, and encourage patients to record headache frequency and drug use (e.g., by keeping a headache diary) [see Warnings and Precautions (5.6)].

Local Irritation

Advise patients to notify their healthcare provider if they have bothersome local irritation [see Warning and Precautions (5.9)].

Drug Interactions

Advise patients to inform their healthcare providers if they are taking, or plan to take, any prescription or over-the-counter drugs, since there is a potential for interactions [see Drug Interactions (7)].

Pregnancy

Advise patients of the risk for preterm birth. Advise women to inform their healthcare provider if they are pregnant or intend to become pregnant [see Warnings and Precautions (5.7), Use in Specific Populations (8.1)].

Lactation

Advise patients not to breastfeed during treatment with ATZUMI [see Use In Specific Populations (8.2)].

Administration Instructions

Instruct patients not to squeeze ATZUMI before inserting it into the nostril because priming is not required. Inform patients that they will need to squeeze the air pump on the ATZUMI device three separate times into one nostril to give a dose. Instruct the patient to squeeze while inhaling, release to allow the air pump to expand back to its original shape, then repeat two more times [see Instructions for Use]. Tell patients to use fast, complete, pulse-like squeezes to deliver their dose. [see Dosage and Administration (2.3)].

Manufactured for Satsuma Pharmaceuticals, Inc., 4819 Emperor Blvd., Suite 340, Durham, NC 27703

© 2025. Satsuma Pharmaceuticals, Inc. All rights reserved.
ATZUMI is a trademark of Satsuma Pharmaceuticals, Inc.

MEDICATION GUIDE
ATZUMI™ (at zoo' mee)
(dihydroergotamine)
nasal powder

What is the most important information I should know about ATZUMI?
ATZUMI can cause serious side effects, including:

- Serious problems with blood circulation to your legs and feet (peripheral ischemia). ATZUMI can cause peripheral ischemia when you take it with certain medicines known as CYP3A4 inhibitors. Peripheral ischemia may lead to a stroke and death. Stop taking ATZUMI and get emergency medical help right away if you have any of the following symptoms:
  - cramping and pain in your legs or hips
  - feeling of heaviness or tightness in your leg muscles
  - burning or aching pain in your feet or toes while resting
  - numbness, tingling, or weakness in your legs
  - cold feeling or color changes in 1 or both legs or feet
  - slurred speech
  - sudden weakness

Do not take medicines known as strong CYP3A4 inhibitors, such as:

- ritonavir
- nelfinavir

- erythromycin
- clarithromycin

- ketoconazole
- itraconazole

These are not all of the medicines that could affect how ATZUMI works. Your healthcare provider can tell you if it is safe to take ATZUMI with other medicines.

What is ATZUMI?
ATZUMI is a prescription medicine used for the acute treatment of migraine with or without aura in adults.

- ATZUMI is not used to prevent migraine.
- ATZUMI is not used to treat other types of headaches such as hemiplegic (that make you unable to move on one side of your body) or basilar (rare form of migraine with aura) migraines.

It is not known if ATZUMI is safe and effective in children.

Who should not take ATZUMI?
Do not take ATZUMI if you:

- are taking medicines known as strong CYP3A4 inhibitors.
- have heart problems or a history of heart problems.
- have uncontrolled high blood pressure.
- have narrowing of blood vessels in your legs, arms, stomach, or kidneys (peripheral vascular disease).
- have sepsis.
- have had vascular surgery.
- have severe liver problems.
- have severe kidney problems.
- are allergic to dihydroergotamine, ergot alkaloids, or any of the ingredients in ATZUMI. See the end of this Medication Guide for a complete list of ingredients in ATZUMI.
- have taken any of the following medicines in the last 24 hours:
  - sumatriptan
  - almotriptan
  - eletriptan
  - frovatriptan
  - naratriptan
  - rizatriptan
  - zolmitriptan
  - ergotamine or ergotamine-type medicines
- have taken any medicines that constrict your blood vessels or raise your blood pressure.

Ask your healthcare provider if you are not sure if you are taking any of these medicines.
Your healthcare provider can tell you if it is safe to take ATZUMI with other medicines.

Before you take ATZUMI, tell your healthcare provider about all of your medical conditions, including if you:

- have high blood pressure.
- have liver problems.
- have kidney problems.
- have risk factors for heart disease. You have a higher risk for heart disease if you:
  - have high blood pressure
  - have high cholesterol levels
  - smoke
  - are overweight
  - have diabetes
  - have a family history of heart disease
- are taking medicines known as strong CYP3A4 inhibitors.
- are pregnant or plan to become pregnant. ATZUMI may cause preterm labor. ATZUMI should be avoided during pregnancy. Talk to your healthcare provider right away if you are pregnant or want to become pregnant.
- are breastfeeding or plan to breastfeed. ATZUMI may reduce breast milk supply and pass into your breast milk. ATZUMI may be harmful to your baby. Do not breastfeed your baby while taking ATZUMI and for 3 days after you use ATZUMI. Talk with your healthcare provider about the best way to feed your baby if you take ATZUMI.

Tell your healthcare provider about all the medicines you take, including prescription and over-the-counter medicines, vitamins, and herbal supplements. Your healthcare provider will decide if you can take ATZUMI with your other medicines.

How should I take ATZUMI?

- ATZUMI is for nasal use only (use in the nose).
- Certain people should take their first dose of ATZUMI in their healthcare provider's office or in another medical setting. Ask your healthcare provider if you should take your first dose in a medical setting.
- Use ATZUMI exactly as your healthcare provider tells you to use it. Read and follow the instructions in the Instructions for Use or use the Quick Reference Guide located on the ATZUMI protective foil pouch.
- If your headache comes back after the first complete dose or you only get some relief from your headache, you can use a second dose 1 hour after the first complete dose. Use a new ATZUMI nasal powder device for the second dose, if needed.
- Do not take more than 2 doses of ATZUMI within a 24-hour period. It is not known if it is safe to take more than 4 doses of ATZUMI in a 7-day period or 12 doses in a 30-day period.
- Taking ATZUMI for 10 or more days in 1 month may make your headaches worse. You should write down when you have headaches and when you take ATZUMI so that you can talk with your healthcare provider about how ATZUMI is working for you. See "What are the possible side effects of ATZUMI?".

If you use too much ATZUMI, call your healthcare provider or Poison Help line at 1-800-222-1222, or go to the nearest hospital emergency room right away.

What are the possible side effects of ATZUMI?
ATZUMI can cause serious side effects, including:
See "What is the most important information I should know about ATZUMI?"

- Heart attack and other heart problems. Heart problems may lead to death. Stop taking ATZUMI and get emergency medical help right away if you have any of the following symptoms of a heart attack:
  - discomfort in the center of your chest that lasts for more than a few minutes, or that goes away and comes back
  - severe tightness, pain, pressure, or heaviness in your chest, throat, neck, or jaw
  - pain or discomfort in your arms, back, neck, jaw, or stomach
  - shortness of breath with or without chest discomfort
  - breaking out in a cold sweat
  - feeling lightheaded
  - nausea or vomiting

ATZUMI is not for people with risk factors for heart disease unless a heart exam is done and shows no problem. See "Before you take ATZUMI, tell your healthcare provider about all of your medical conditions, including if you:" for the risk factors for heart disease.

- Stroke. Stop taking ATZUMI and get emergency medical help right away if you have any of the following symptoms of a stroke:
  - face drooping
  - unusual weakness or numbness
  - slurred speech
- Changes in color or sensation in your fingers and toes (Raynaud's syndrome).
- Stomach and intestinal problems (gastrointestinal and colonic ischemic events). Symptoms of gastrointestinal and colonic ischemic events include:
  - sudden or severe stomach pain
  - constipation or diarrhea
  - stomach pain after meals
  - bloody diarrhea
  - weight loss
  - fever
  - nausea or vomiting
- Increased blood pressure.
- Medicine overuse headache. Some people who use too much ATZUMI may make their headaches worse (medicine overuse headache). If your headaches get worse, your healthcare provider may decide to stop your treatment with ATZUMI.
- Preterm labor.
- Tissue changes (fibrotic complications). Inflammation and fiber-like tissue that is not normal (fibrosis) can occur around the lungs and stomach.
- Nose irritation. Discomfort in your nose, change in taste, stuffy nose, and cold-type symptoms, (such as, runny nose, sneezing, and cough) can occur.

The most common side effects of ATZUMI include:

- runny nose
- nausea
- abnormal taste

- application site reactions
- dizziness
- vomiting

- sleepiness
- sore throat
- diarrhea

These are not all of the possible side effects of ATZUMI.
Call your doctor for medical advice about side effects. You may report side effects to FDA at 1-800-FDA-1088.

How should I store ATZUMI?

- Store ATZUMI at room temperature between 68°F to 77°F (20°C to 25°C).
- Store ATZUMI in its protective foil pouch until ready to use.

Keep ATZUMI and all medicines out of the reach of children.

General information about the safe and effective use of ATZUMI.
Medicines are sometimes prescribed for purposes other than those listed in a Medication Guide. Do not use ATZUMI for a condition for which it was not prescribed. Do not give ATZUMI to other people, even if they have the same symptoms you have. It may harm them. You can ask your pharmacist or healthcare provider for information about ATZUMI that is written for health professionals.

What are the ingredients in ATZUMI?
Active ingredient: Dihydroergotamine
Inactive ingredients: Hypromellose, mannitol, and microcrystalline cellulose
ATZUMI is a trademark of Satsuma Pharmaceuticals, Inc.
Manufactured for Satsuma Pharmaceuticals, Inc., Durham, NC 27703
© 2025. Satsuma Pharmaceuticals, Inc. All rights reserved.
For more information, go to www.atzumi.com or call 1-888-273-2480.

This Medication Guide has been approved by the U.S. Food and Drug Administration.

Issued: 04/2025

INSTRUCTIONS FOR USE

ATZUMI™ (at zoo' mee)
(dihydroergotamine)
nasal powder

For Nasal Use Only

This Instructions for Use contains information on how to use ATZUMI.

Read this Instructions for Use before using ATZUMI.

Important Information You Need to Know Before Using ATZUMI

- ATZUMI contains 1 complete dose of medicine and should be thrown away after each use.
- ATZUMI is for nasal (nose) use only.
- Deliver all the powdered medicine into only 1 nostril.
- Do not use ATZUMI if it is damaged or expired.
- Do not squeeze ATZUMI before inserting it into the nostril. Priming is not required.
- Powdered medicine is inside the blue nozzle. When you squeeze the white air pump, air is pushed into the blue nozzle and pushes the powdered medicine into your nose.
- Do not squeeze slowly, partially or with any hesitation. When dosing, you must fully squeeze the white air pump as fast as you can. A fast, pulse-like squeezing action is needed.

How often can you use ATZUMI?

- If needed, you may take a second dose 1 hour after your first dose. Wait at least 1 hour before taking the second dose.
- Do not take more than 2 doses within a 24-hour period.
- It is not known if it is safe to take more than 4 doses of ATZUMI in a 7-day period or 12 doses in a 30-day period.

Storing ATZUMI

- Store ATZUMI at room temperature between 68°F to 77°F (20°C to 25°C).
- Store ATZUMI in its protective foil pouch until ready to use (Figure C).
- Keep ATZUMI and all medicines out of the reach of children.

Step 1. Preparing to Use ATZUMI

1.1 Blow Your Nose
  Blow your nose to clear your nostrils (Figure D).
1.2 Take Out ATZUMI Open the protective foil pouch by tearing at the notch.
  Remove ATZUMI from the protective foil pouch (Figure E).
1.3 Check ATZUMICheck the Expiration Date to make sure ATZUMI is not expired (Figure F).
  Check ATZUMI for damage.
  If ATZUMI is expired or damaged, throw it away in your household trash and get a new ATZUMI.
1.4 Remove Clear Cap Pull the clear cap straight off (Figure G).

Step 2. Using ATZUMI

2.1 Remove Round Blue Tab Hold the nozzle base in 1 hand.
  Remove the round blue tab by bending it back and forth or twisting it to break it off (Figure H).
  This creates an opening for the powdered medicine to pass through.
  Important: Do not squeeze the white air pump yet. Wait until Step 2.3.
2.2 Insert Into Nostril Hold the white air pump as shown in Figure I and insert the blue nozzle into 1 nostril as far as it will comfortably go. The nozzle base should touch your nose (Figure I).
2.3 Deliver All of the Powdered Medicine into Only 1 Nostril
• Squeeze the white air pump 3 separate times into 1 nostril. Inhale through your nose each time you squeeze (Figure J).
• Fast, complete, pulse-like squeezes are needed to push the powdered medicine and deliver the complete dose.
• Do not squeeze slowly, partially or with any hesitation.
• Allow the white air pump to expand back to its original shape between squeezes (Figure J). Important:
  Deliver all the powdered medicine into only 1 nostril.

Step 3. Inspecting ATZUMI

3.1 Check for Remaining Powdered Medicine
• Keep ATZUMI upright and look inside the blue nozzle to see if any loose powdered medicine remains at the bottom (Figure K).
• If loose powdered medicine remains, repeat Step 2.3 to dose into the same nostril, but squeeze the white air pump faster. Repeat Step 2.3 until no loose powdered medicine remains.
  Note:
• It is normal to see a light coating of powdered medicine in the blue nozzle after delivering the complete dose.
• If you are not sure whether you have delivered all of the loose powdered medicine, then repeat Step 2.3 with the same ATZUMI device in the same nostril.

Step 4. Throwing Away ATZUMI

After use, throw away the protective foil pouch, the ATZUMI device, the round blue tab, and the clear cap in your household trash (Figure L).
  Do not save ATZUMI after use. ATZUMI contains a one-time (single) dose.

This Instructions for Use has been approved by the U.S. Food and Drug Administration.
Approved: 4/2025

Quick Reference Guide

This is a Quick Reference Guide. Read the full Instructions for Use before using ATZUMI. Deliver ATZUMI into only 1 nostril.

1. Blow your nose to clear your nostrils.
2. Pull the clear cap straight off.
3. Twist or bend the round blue tab to break it off.
4. Insert the blue nozzle all the way into your nostril.
5. Squeeze the white air pump 3 separate times into 1 nostril. Inhale through your nose each time you squeeze. Fast, complete, pulse-like squeezes are needed. Do not squeeze slowly, partially or with hesitation.
  Allow the white air pump to expand back to its original shape between squeezes.
  Deliver all of the powdered medicine into only 1 nostril.
6. Check inside the blue nozzle. If loose powdered medicine remains, repeat Step 5 with the same ATZUMI device in the same nostril, but with a faster squeeze.
7. Throw away ATZUMI in your household trash. ATZUMI is for one-time (single) use only.

This Quick Reference Guide has been approved by the U.S. Food and Drug Administration.
Approved: 04/2025

PRINCIPAL DISPLAY PANEL - 5.2 mg Bottle Carton

Atzumi™
(dihydroergotamine)
nasal powder

5.2 mg

For nasal use only.
Discard after use.
Contains:

- 8 preﬁlled single-dose devices
- Instructions for Use
- Medication Guide
- Prescribing Information

Nasal devices not for individual sale.
Dispense entire carton and accompanying Medication Guide to each patient.

Rx Only
NDC 76978-101-08

© 2025 Satsuma Pharmaceuticals, Inc. All rights reserved.

PRINCIPAL DISPLAY PANEL - 5.2 mg Device Pouch Label

Atzumi™
(dihydroergotamine)
nasal powder

5.2 mg

For nasal use only.
Discard after use.
Recommended Dosage: See Prescribing
Information.
Contains 1 prefilled single-dose device.
Nasal devices not for individual sale.
Store ATZUMI in its protective pouch at room
temperature 68°F to 77°F (20°C to 25°C).
Excursions allowed between 59°F to 86°F
(15°C to 30°C).

Keep out of reach of children.
INSTRUCTIONS
ON REVERSE

Rx Only
NDC 76978-101-01

Manufactured for
Satsuma Pharmaceuticals, Inc.
Durham, NC 27703

© 2025 Satsuma Pharmaceuticals, Inc. All rights reserved.